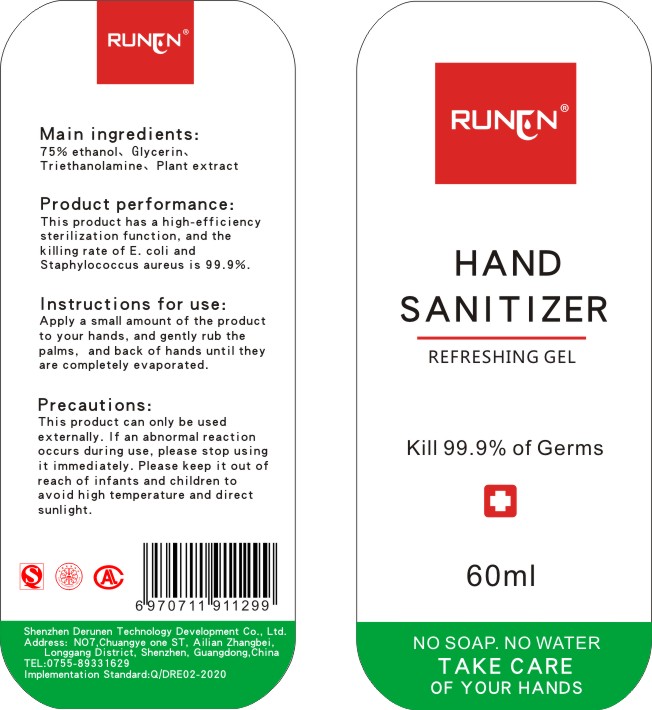 DRUG LABEL: HAND SANITIZER
NDC: 55029-001 | Form: LIQUID
Manufacturer: Shenzhen Derun'en Science & Technology Development Co., Ltd
Category: otc | Type: HUMAN OTC DRUG LABEL
Date: 20200407

ACTIVE INGREDIENTS: ALCOHOL 45 mL/60 mL; 1-O-TETRADECYLGLYCEROL 0.6 mg/60 mL
INACTIVE INGREDIENTS: CARBOMER HOMOPOLYMER, UNSPECIFIED TYPE

DOSAGE AND ADMINISTRATION

a little

INACTIVE INGREDIENT

carbomer

ACTIVE INGREDIENT

Absolute ethanol

glycerin

keep out of children

PURPOSE

Kill 99.9% of Germs

INDICATIONS AND USAGE

Apply a small amount of the product to your hands, and gently rub the palms，and back of hands until they are completely evaporated.

WARNINGS

This product can only be used externally. If an abnormal reaction occurs during use, please stop using it immediately. Please keep it out of reach of infants and children to avoid high temperature and direct sunlight.